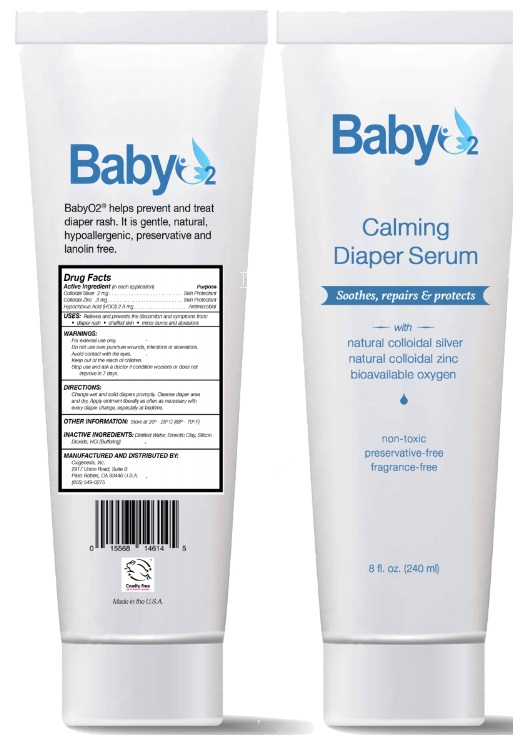 DRUG LABEL: BabyO2
NDC: 72136-007 | Form: LIQUID
Manufacturer: Oxigenesis, Inc.
Category: otc | Type: HUMAN OTC DRUG LABEL
Date: 20200917

ACTIVE INGREDIENTS: SILVER 48 mg/240 mL; ZINC 6 mg/240 mL; HYPOCHLOROUS ACID 65.8 mg/240 mL
INACTIVE INGREDIENTS: WATER; LAPONITE; SILICON DIOXIDE; HYDROCHLORIC ACID

Active Ingredient Purpose

Colloidal Silver 48 mg ................................................ Skin Protectant
Colloidal Zinc 6 mg .................................................... Skin Protectant
HOCl 66 mg ............................................................... Antimicrobial

Uses

Relieves and prevents the discomfort and symptoms from: diaper rash, chaffed skin, minor burns and abrasions.

Warnings

- For external use only.
- Do not use over puncture wounds, infections or lacerations. Avoid contact with the eyes. Stop use and ask a doctor if condition worsens or does not improve in 7 days.

Keep out of reach of children.

Directions

Change wet and solid diapers promptly. Cleanse diaper area and dry. Apply serum liberally as often necessary with every diaper change, especially at bedtime.

Other information
Store at 20°-25°C (68° -70° F)

Inactive ingredients

Distilled water, Smectic Clay, Silicon Dioxide, HCl (buffering)